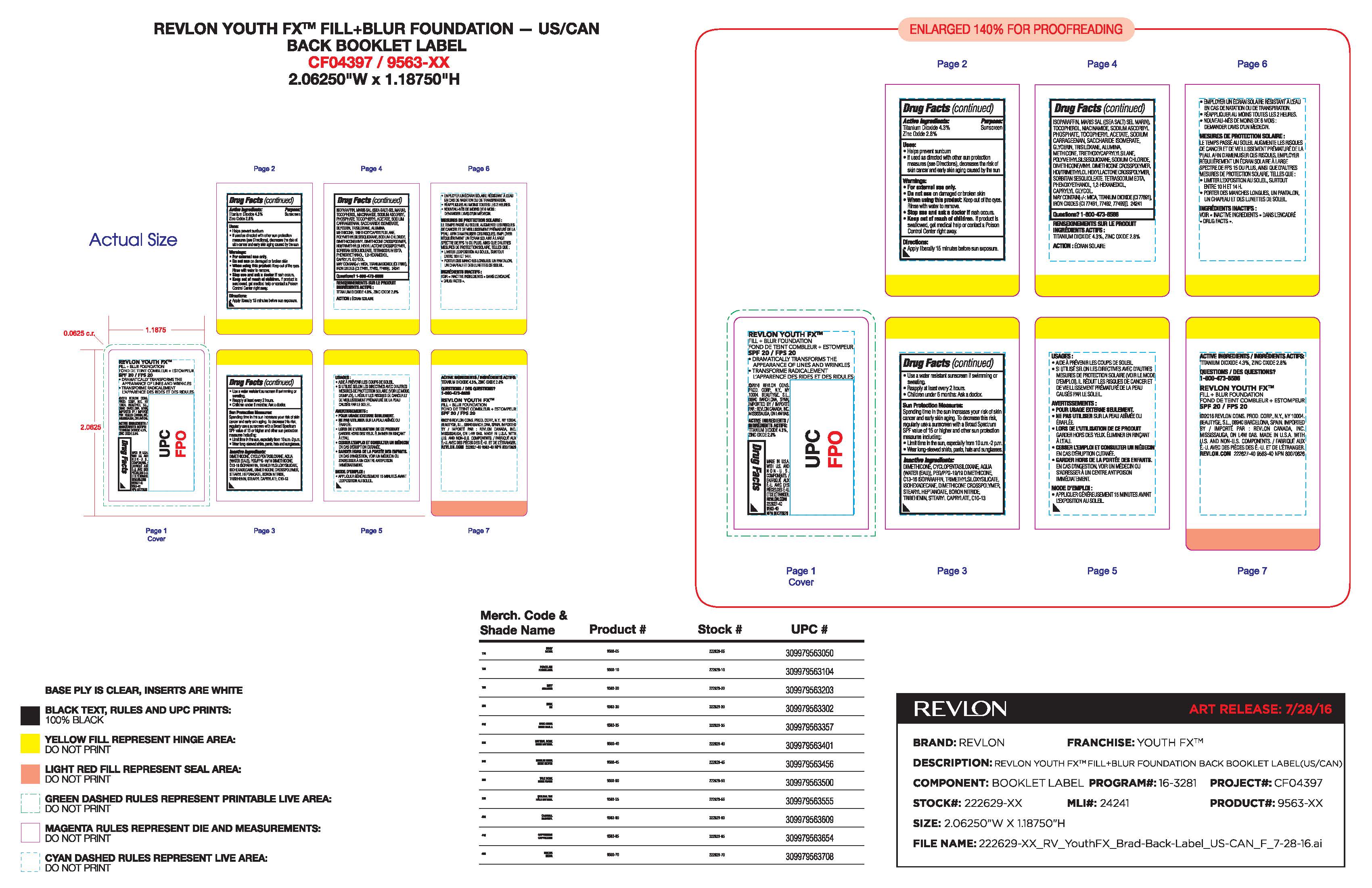 DRUG LABEL: Revlon Youth FX
NDC: 10967-639 | Form: LIQUID
Manufacturer: Revlon Consumer Products Corp
Category: otc | Type: HUMAN OTC DRUG LABEL
Date: 20241231

ACTIVE INGREDIENTS: ZINC OXIDE 2.8 mg/30 mL; TITANIUM DIOXIDE 4.3 mg/30 mL
INACTIVE INGREDIENTS: WATER; DIMETHICONE; CYCLOMETHICONE 5; PEG/PPG-19/19 DIMETHICONE; GLYCERIN; C13-16 ISOPARAFFIN; TRIMETHYLSILOXYSILICATE (M/Q 1.0-1.2); ISOHEXADECANE; STEARYL HEPTANOATE; BORON NITRIDE; TRIBEHENIN; SEA SALT; TOCOPHEROL; NIACINAMIDE; SODIUM ASCORBYL PHOSPHATE; .ALPHA.-TOCOPHEROL ACETATE; SACCHARIDE ISOMERATE; TRISILOXANE; ALUMINUM OXIDE; METHICONE (20 CST); TRIETHOXYCAPRYLYLSILANE; POLYMETHYLSILSESQUIOXANE (11 MICRONS); SODIUM CHLORIDE; DIMETHICONE/VINYL DIMETHICONE CROSSPOLYMER (HARD PARTICLE); SORBITAN SESQUIOLEATE; EDETATE SODIUM; PHENOXYETHANOL; 1,2-HEXANEDIOL; CAPRYLYL GLYCOL

Revlon Youth FX Fill + Blur Foundation

Active Ingredients:

Titanium Dioxide 4.3%

Zinc Oxide 2.8

Purpose:

Sunscreen

Uses:

- Helps prevent sunburn
- If used as directed with other sun protection measures (see Directions), decreases the risk of skin cancer and early skin aging caused by the sun

Warnings:

- For external use only
- Do notuse on damaged or broken skin
- When using this product: Keep out of eyes. Rinse with water to remove.
- Stop use and ask a doctor if a rash occurs
- Keep out of reach of children. If product is swallowed, get medical help or contact a Poison Control center right away

Directions:

- Apply liberally 15 minutes before sun exposure
- Use a water resistant sunscreen if swimming or sweating
- Reapply at least every 2 hours
- Children under 6 months: Ask a doctor.

Sun Protection Measures:

Spending time in the sun increases your risk of skin cancer and early skin aging. To decrease this risk, regularly use a sunscreen with a Broad Spectrum SPF value of 15 or higher and other sun protection measures including:

- Limit time in the sun, especially from 10 am - 2 pm
- Wear long-sleeved shirts, pants, hats and sunglasses.

Inactive Ingredients:

Dimethicone, Cyclopentasiloxane, Aqua (Water (Eau)), PEG/PPG-19/19 Dimethicone, C13-16 Isoparaffin, Trimethylsiloxysilicate, Isohexadecane, Dimethicone Crosspolymer, Stearyl Heptanoate, Boron Nitride, Tribehenin, Stearyl Caprylate, C10-13 Isoparaffin, Maris Sal ((Sea Salt) Sel Marin), Tocopherol, Niacinamide, Sodium Ascorbyl Phosphate, Tocopheryl Acetate, Sodium Carrageenan, Saccharide Isomerate, Glycerin, Trisiloxane, Alumina, Methicone, Triethoxycaprylylsilane, Polymethylsilsesquioxane, Sodium Chloride, Dimethicone/Vinyl Dimethicone Crosspolymer, HDI/Trimethylol Hexyllactone Crosspolymer, Sorbitan Sesquioleate, Tetrasodium EDTA, Phenoxyethanol, 1,2-Hexanediol, Caprylyl Glycol

May Contain Mica, Titanium Dioxide (Ci 77891), Iron Oxides (CI 77491, 77492, 77499)

DOSAGE AND ADMINISTRATION

Apply liberally 15 minutes before sun exposure.

KEEP OUT OF REACH OF CHILDREN

Keep out of the reach of children. If product is swallowed, get medical help or contact a Poison Control Center right away.

PURPOSE

Sunscreen

Principal Display Panel:

REVLON

Revlon Youth FX Fill + Blur Foundation

1.0 fL. OZ/30 mL